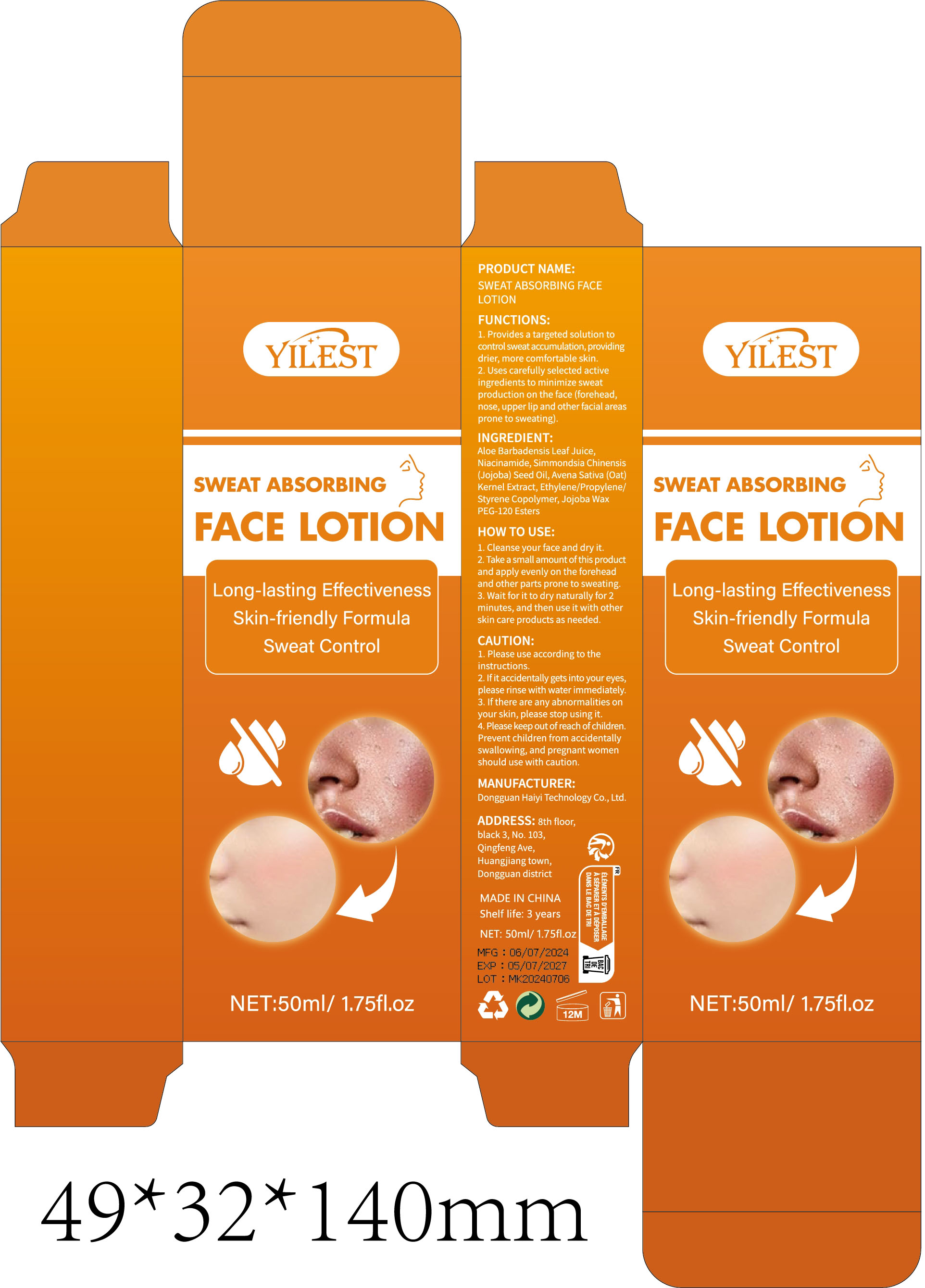 DRUG LABEL: Antiperspirant moisturizer
NDC: 84732-038 | Form: CREAM
Manufacturer: Dongguan Haiyi Technology Co.,Ltd.
Category: otc | Type: HUMAN OTC DRUG LABEL
Date: 20241010

ACTIVE INGREDIENTS: ALOE VERA LEAF 1 mg/50 mL
INACTIVE INGREDIENTS: NIACINAMIDE; ETHYLENE; JOJOBA OIL; HYDROGENATED JOJOBA OIL/JOJOBA OIL, RANDOMIZED (IODINE VALUE 64-70); OAT

Active ingredient

Aloe Barbadensis Leaf Juice

Inactive ingredient

Niacinamide,Simmondsia Chinensis (Jojoba) Seed Oil, Avena Sativa (Oat) Kernel Extract, Ethylene/Propylene Styrene Copolymer, Jojoba Wax PEG-120 Esters

Purpose section

1. Provides a targeted solution tocontrol sweat accumulation, providingdrier, more comfortable skin.

2. Uses carefully selected activeingredients to minimize sweatproduction on the face (forehead,nose, upper lip and other facial areasprone to sweating)

Warning

1. Please use according to theinstructions.

2. lf it accidentally gets into your eyes,please rinse with water immediately.

3. lf there are any abnormalities onyour skin, please stop using it.

4. Please keep out of reach of children.Prevent children from accidentallyswallowing, and pregnant womenshould use with caution.

stop use

This product may cause allergic reactions in asmall number of people.
lf youexperience any discomfort,please stop using it immediately.

not use

Not suitable for use by children, pregnantor breast feeding people.

OUT OF CHILDREN

KEEP THE PRODUCT OUT OF REACH OF CHILDREN to

HOW TO USE

1. Cleanse your face and dry it.

2. Take a small amount ofthis productand apply evenly on the foreheadand other parts prone to sweating

3. Wait for it to dry naturally for 2minutes, and then use it with otherskin care products as needed

Dosage

take an appropriateamount,Use 2-3 times a week